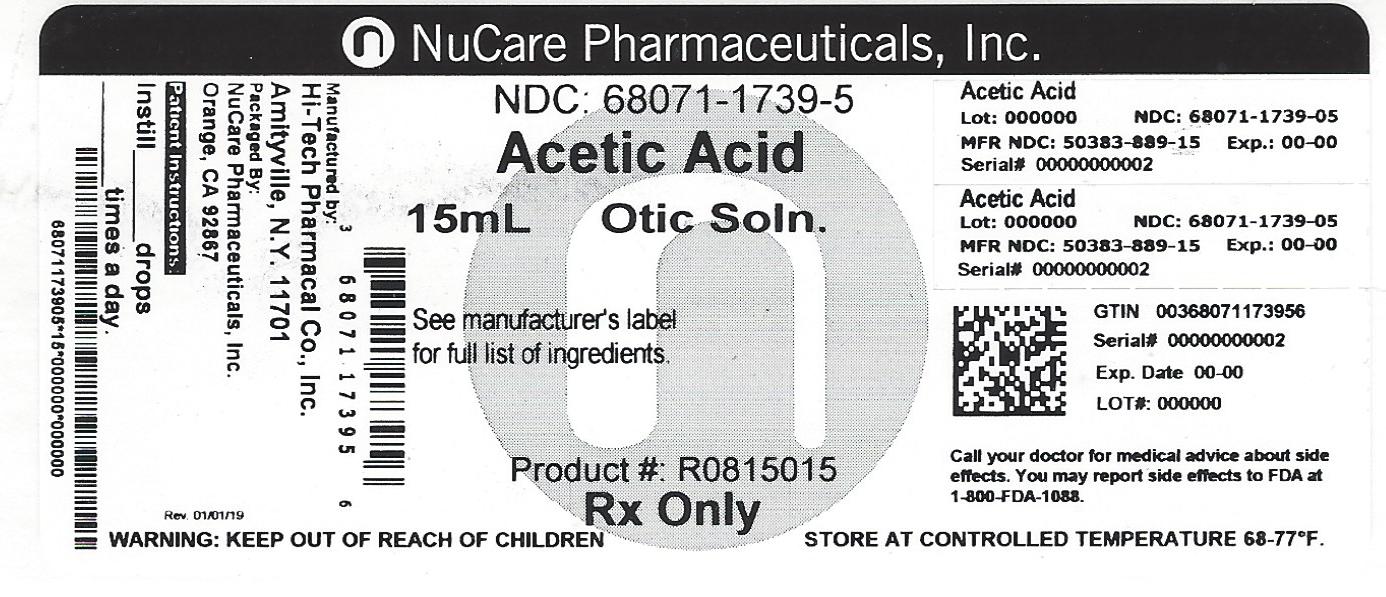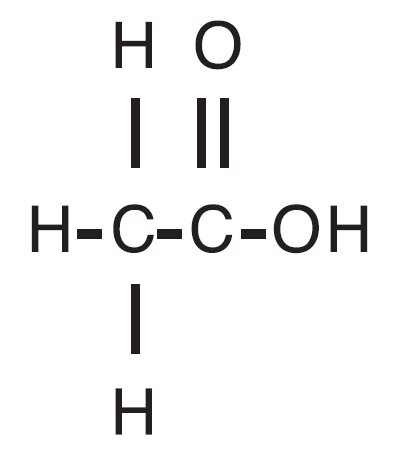 DRUG LABEL: Acetic Acid
NDC: 68071-1739 | Form: SOLUTION
Manufacturer: NuCare Pharmaceuticals,Inc.
Category: prescription | Type: HUMAN PRESCRIPTION DRUG LABEL
Date: 20240715

ACTIVE INGREDIENTS: ACETIC ACID 20.65 mg/1 mL
INACTIVE INGREDIENTS: PROPYLENE GLYCOL; BENZETHONIUM CHLORIDE; PROPYLENE GLYCOL DIACETATE; SODIUM ACETATE

Acetic Acid Otic Solution, USP

DESCRIPTION

Acetic Acid Otic Solution, USP is a solution of acetic acid (2%) in a propylene glycol vehicle containing propylene glycol diacetate (3%), benzethonium chloride (0.02%), and sodium acetate (0.015%). The empirical formula for acetic acid is CH3COOH, with a molecular weight of 60.05. The structural formula is:

Acetic Acid is available as a nonaqueous otic solution buffered at pH 3 for use in the external ear canal.

CLINICAL PHARMACOLOGY

Acetic acid is antibacterial and antifungal; propylene glycol is hydrophilic and provides a low surface tension; benzethonium chloride is a surface active agent that promotes contact of the solution with tissues.

INDICATIONS AND USAGE

For the treatment of superficial infections of the external auditory canal caused by organisms susceptible to the action of the antimicrobial.

CONTRAINDICATIONS

Hypersensitivity to acetic acid or any of the ingredients. Perforated tympanic membrane is considered a contraindication to the use of any medication in the external ear canal.

WARNINGS

Discontinue promptly if sensitization or irritation occurs.

PRECAUTIONS

Transient stinging or burning may be noted occasionally when the solution is first instilled into the acutely inflamed ear.

PEDIATRIC USE

Safety and effectiveness in pediatric patients below the age of 3 years have not been established.

ADVERSE REACTIONS

Stinging or burning may be noted occasionally; local irritation has occurred very rarely.

DOSAGE AND ADMINISTRATION

Carefully remove all cerumen and debris to allow acetic acid to contact infected surfaces directly. To promote continuous contact, insert a wick of cotton saturated with acetic acid into the ear canal; the wick may also be saturated after insertion. Instruct the patient to keep the wick in for at least 24 hours and to keep it moist by adding 3 to 5 drops of acetic acid every 4 to 6 hours. The wick may be removed after 24 hours but the patient should continue to instill 5 drops of acetic acid 3 or 4 times daily thereafter, for as long as indicated. In pediatric patients, 3 to 4 drops may be sufficient due to the smaller capacity of the ear canal.

HOW SUPPLIED

Acetic Acid Otic Solution, USP, containing 2% acetic acid, is available in 15 mL NDC 68071-1739-5 measured-drop, safety-tip plastic bottles.

STORAGE

Store at 20°- 25°C (68°-77°F). Keep container tightly closed.

Hi-Tech Pharmacal Co., Inc.

Amityville, NY 11701

Rev. 889:02 11/09